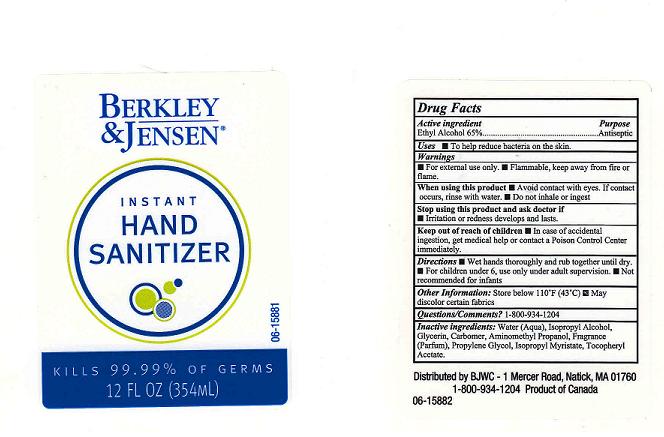 DRUG LABEL: INSTANT HAND SANITIZER
NDC: 68391-267 | Form: GEL
Manufacturer: BJWC
Category: otc | Type: HUMAN OTC DRUG LABEL
Date: 20110106

ACTIVE INGREDIENTS: ALCOHOL 65 mL/100 mL
INACTIVE INGREDIENTS: WATER; ISOPROPYL ALCOHOL; GLYCERIN; CARBOMER 934; AMINOMETHYLPROPANOL; PROPYLENE GLYCOL; ISOPROPYL MYRISTATE; .ALPHA.-TOCOPHEROL ACETATE, D-

DRUG FACTS

ACTIVE INGREDIENT

ETHYL ALCOHOL 65 PERCENT

PURPOSE

ANTISEPTIC

USES

TO HELP REDUCE BACTERIA ON THE SKIN.

WARNINGS

FOR EXTERNAL USE ONLY. FLAMMABLE, KEEP AWAY FROM FIRE OR FLAME.

WHEN USING THIS PRODUCT

AVOID CONTACT WITH EYES.IF CONTACT OCCURS, RINSE WITH WATER. DO NOT INHALE OR INGEST.

STOP USING THIS PRODUCT AND ASK DOCTOR IF

IRRITATION OR REDNESS DEVELOPS AND LASTS.

KEEP OUT OF REACH OF CHILDREN

IN CASE OF ACCIDENTAL INGESTION, GET MEDICAL HELP OR CONTACT A POISON CONTROL CENTER IMMEDIATELY.

DIRECTIONS

WET HANDS THOROUGHLY AND RUB TOGETHER UNTIL DRY. FOR CHILDREN UNDER 6, USE ONLY UNDER ADULT SUPERVISION. NOT RECOMMENDED FOR INFANTS.

OTHER INFORMATION

STORE BELOW 110^0F (43^0C). MAY DISCOLOR CERTAIN FABRICS.

QUESTIONS OR COMMENTS

1-800-934-1204

INACTIVE INGREDIENTS

WATER, ISOPROPYL ALCOHOL, GLYCERIN, CARBOMER, AMINOMETHYL PROPANOL, FRAGRANCE, PROPYLENE GLYCOL, ISOPROPYL MYRISTATE, TOCOPHERYL ACETATE.